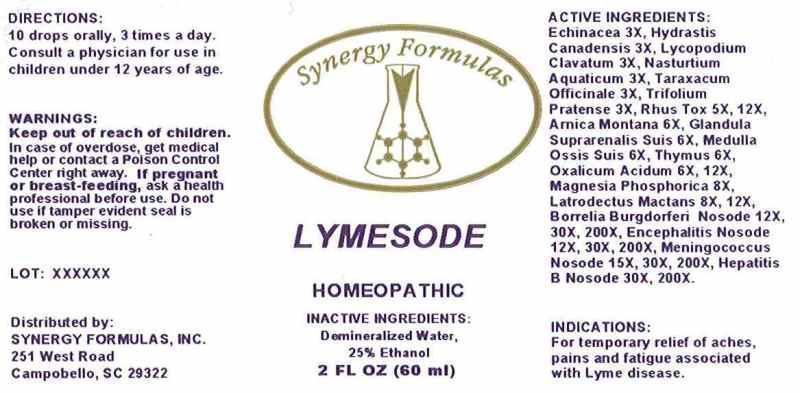 DRUG LABEL: Lymesode
NDC: 43772-0038 | Form: LIQUID
Manufacturer: Synergy Formulas, Inc.
Category: homeopathic | Type: HUMAN OTC DRUG LABEL
Date: 20140715

ACTIVE INGREDIENTS: ECHINACEA ANGUSTIFOLIA 3 [hp_X]/1 mL; GOLDENSEAL 3 [hp_X]/1 mL; LYCOPODIUM CLAVATUM SPORE 3 [hp_X]/1 mL; NASTURTIUM OFFICINALE 3 [hp_X]/1 mL; TARAXACUM OFFICINALE 3 [hp_X]/1 mL; TRIFOLIUM PRATENSE FLOWER 3 [hp_X]/1 mL; TOXICODENDRON PUBESCENS LEAF 3 [hp_X]/1 mL; ARNICA MONTANA 6 [hp_X]/1 mL; SUS SCROFA ADRENAL GLAND 6 [hp_X]/1 mL; SUS SCROFA BONE MARROW 6 [hp_X]/1 mL; SUS SCROFA THYMUS 6 [hp_X]/1 mL; OXALIC ACID 6 [hp_X]/1 mL; MAGNESIUM PHOSPHATE, DIBASIC TRIHYDRATE 8 [hp_X]/1 mL; LATRODECTUS MACTANS 8 [hp_X]/1 mL; BORRELIA BURGDORFERI 12 [hp_X]/1 mL; JAPANESE ENCEPHALITIS VIRUS 12 [hp_X]/1 mL; NEISSERIA MENINGITIDIS 15 [hp_X]/1 mL; HEPATITIS B VIRUS 30 [hp_X]/1 mL
INACTIVE INGREDIENTS: WATER; ALCOHOL

Drug Facts:

ACTIVE INGREDIENTS:

Echinacea (Angustifolia) 3X, Hydrastis Canadensis 3X, Lycopodium Clavatum 3X, Nasturtium Aquaticum 3X, Taraxacum Officinale 3X, Trifolium Pratense 3X, Rhus Tox 5X, 12X, Arnica Montana 6X, Glandula Suprarenalis Suis 6X, Medulla Ossis Suis 6X, Thymus (Suis) 6X, Oxalicum Acidum 6X, 12X, Magnesia Phosphorica 8X, Latrodectus Mactans 8X, 12X, Borrelia Burgdorferi Nosode 12X, 30X, 200X, Encephalitis Nosode 12X, 30X, 200X, Meningococcus Nosode 15X, 30X, 200X, Hepatitis B Nosode 30X, 200X.

INDICATIONS:

For temporary relief of aches, pains and fatigue associated with Lyme disease.

WARNINGS:

Keep out of reach of children. In case of overdose, get medical help or contact a Poison Control Center right away.

If pregnant or breast-feeding, ask a health professional before use.

Do not use if tamper evident seal is broken or missing.

Keep out of reach of children. In case of overdose, get medical help or contact a Poison Control Center right away.

DIRECTIONS:

10 drops orally, 3 times a day. Consult a physician for use in children under 12 years of age.

INDICATIONS:

For temporary relief of aches, pains and fatigue associated with Lyme disease.

INACTIVE INGREDIENTS:

Demineralized Water, 25% Ethanol

QUESTIONS:

Distributed by:

SYNERGY FORMULAS, INC.

251 West Road

Campobello, SC 29322

PACKAGE LABEL DISPLAY:

Synergy Formulas

LYMESODE

HOMEOPATHIC

2 FL OZ (60 ml)